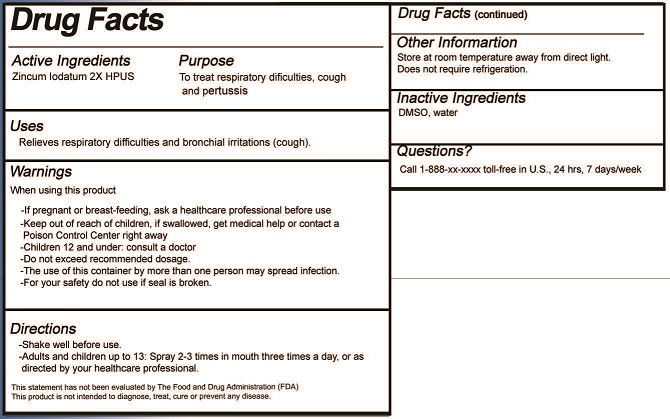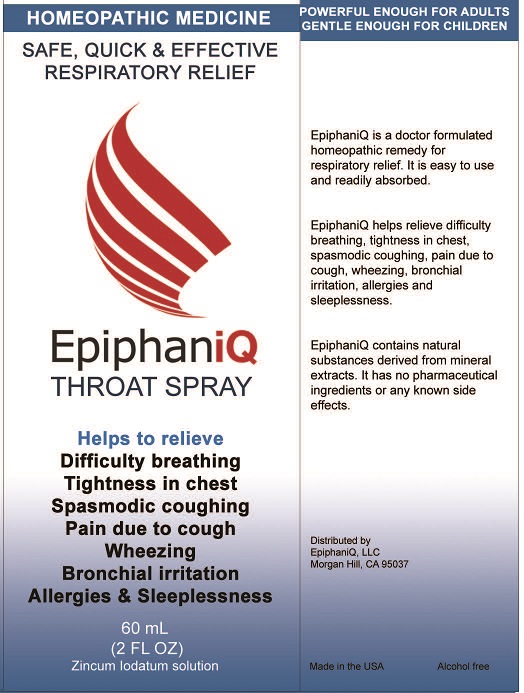 DRUG LABEL: EpiphaniQ Throat
NDC: 79813-202 | Form: SPRAY
Manufacturer: EpiphaniQ LLC
Category: homeopathic | Type: HUMAN OTC DRUG LABEL
Date: 20211229

ACTIVE INGREDIENTS: ZINC IODIDE 2 [hp_X]/100 mL
INACTIVE INGREDIENTS: DIMETHYL SULFOXIDE; WATER

EpiphaniQ Throat Spray (79813-202)

ACTIVE INGREDIENT

ZINCUM IODATUM 2X HPUS

PURPOSE

TO TREAT RESPIRATORY DIFFICULTIES, COUGH AND PERTUSSIS

USES

Relieves respiratory difficulties and bronchial irritations (cough).

WARNINGS

- If pregnant or breast-feeding ask a healthcare professional before use
- Children under 12: consult a doctor before use
- Do not exceed recommended dosage
- The use of this container by more than one person may spread infection
- For your safety do not use if seal is broken

- Keep out of reach of children. In case of overdose, get medical help or contact a Poison Control center right away

DIRECTIONS

- Shake well before use.
- Adults and children up to 13: Spray 2-3 times in mouth three times a day, or as directed by your healthcare professional.

INACTIVE INGREDIENTS

DMSO, WATER

QUESTIONS

CALL TOLL FREE 1-800-XXX-XXXX IN THE U.S., 24 HRS, 7 DAY/WEEK